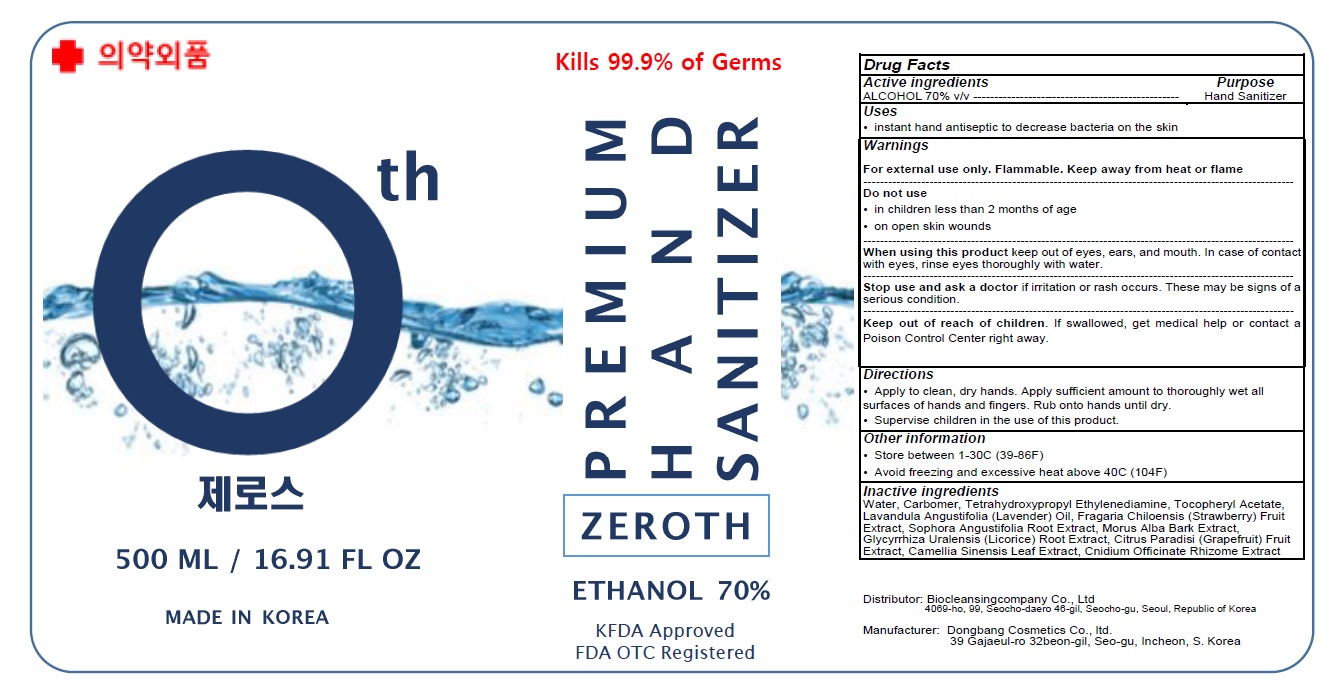 DRUG LABEL: Zeroth premium hand sanitizer
NDC: 78393-010 | Form: GEL
Manufacturer: Biocleansingcompany Co., Ltd
Category: otc | Type: HUMAN OTC DRUG LABEL
Date: 20200527

ACTIVE INGREDIENTS: ALCOHOL 350 mL/500 mL
INACTIVE INGREDIENTS: Water; CARBOMER HOMOPOLYMER, UNSPECIFIED TYPE; EDETOL; .ALPHA.-TOCOPHEROL ACETATE; LAVENDER OIL; BEACH STRAWBERRY; SOPHORA FLAVESCENS ROOT; MORUS ALBA BARK; GLYCYRRHIZA URALENSIS ROOT; GRAPEFRUIT; GREEN TEA LEAF; CNIDIUM OFFICINALE ROOT

ACTIVE INGREDIENT

ALCOHOL 70% v/v

INACTIVE INGREDIENTS

Water, Carbomer, Tetrahydroxypropyl Ethylenediamine, Tocopheryl Acetate, Lavandula Angustifolia (Lavender) Oil, Fragaria Chiloensis (Strawberry) Fruit Extract, Sophora Angustifolia Root Extract, Morus Alba Bark Extract, Glycyrrhiza Uralensis (Licorice) Root Extract, Citrus Paradisi (Grapefruit) Fruit Extract, Camellia Sinensis Leaf Extract, Cnidium Officinate Rhizome Extract

Purpose

Hand Sanitizer

Warnings

For external use only. Flammable. Keep away from heat or flame
--------------------------------------------------------------------------------------------------------
Do not use
• in children less than 2 months of age
• on open skin wounds
--------------------------------------------------------------------------------------------------------
When using this product keep out of eyes, ears, and mouth. In case of contact with eyes, rinse eyes thoroughly with water.
--------------------------------------------------------------------------------------------------------
Stop use and ask a doctor if irritation or rash occurs. These may be signs of a serious condition.

KEEP OUT OF REACH OF CHILDREN

If swallowed, get medical help or contact a Poison Control Center right away.

Uses

• instant hand antiseptic to decrease bacteria on the skin

Directions

• Apply to clean, dry hands. Apply sufficient amount to thoroughly wet all surfaces of hands and fingers. Rub onto hands until dry.
• Supervise children in the use of this product.

Other information

• Store between 1-30C (39-86F)
• Avoid freezing and excessive heat above 40C (104F)